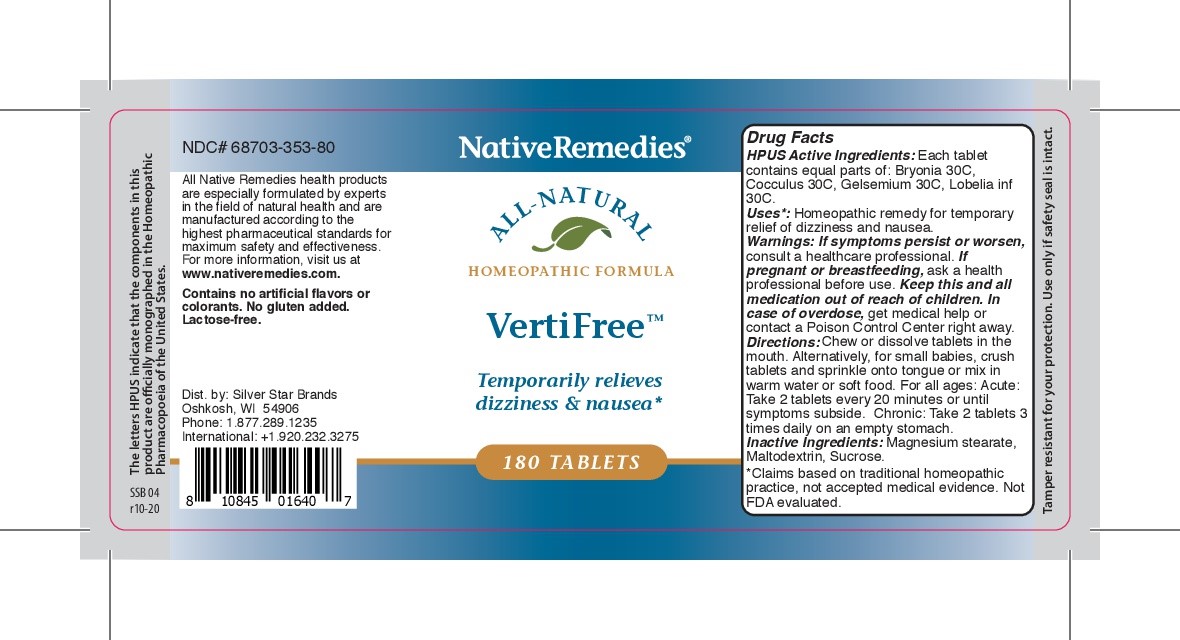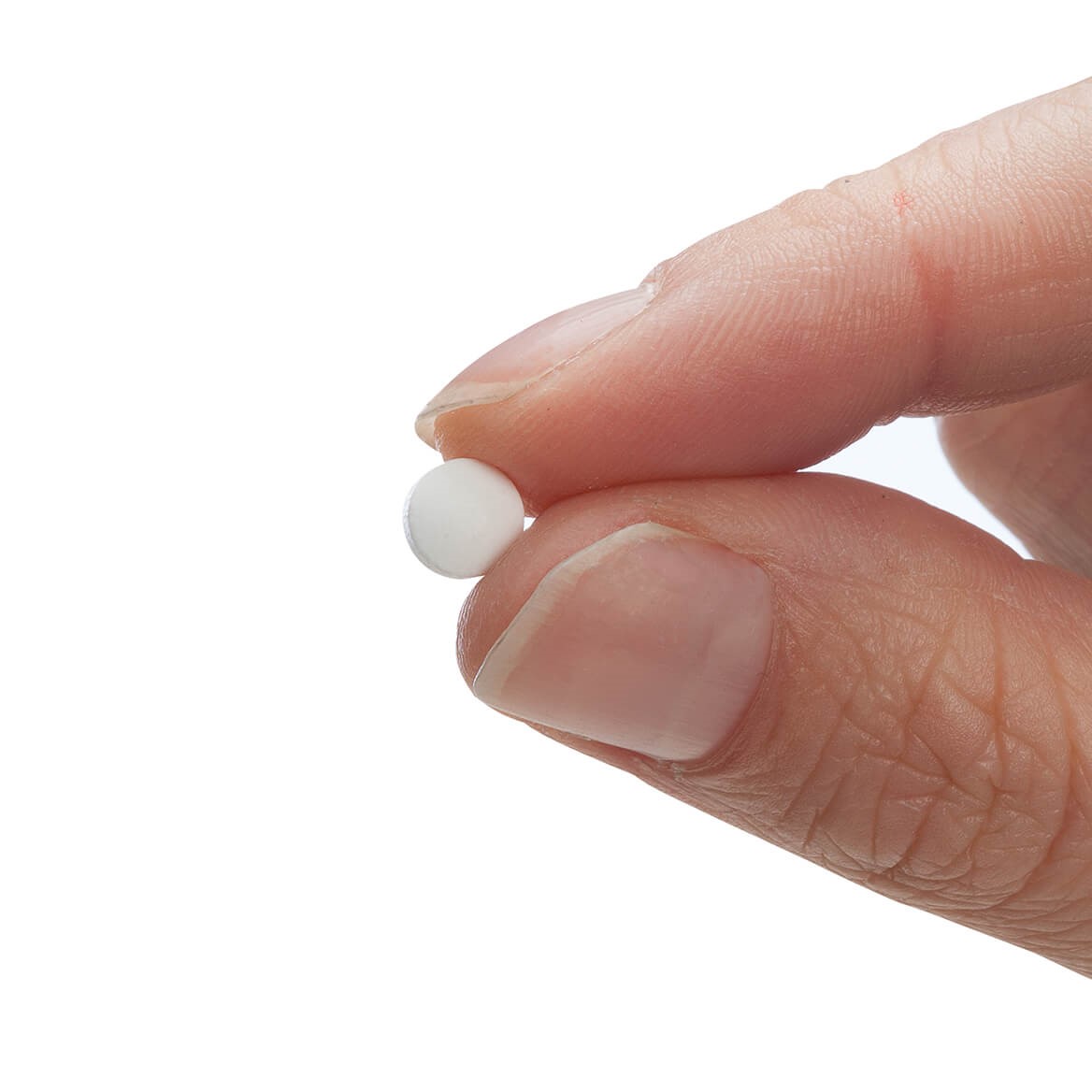 DRUG LABEL: VertiFree
NDC: 68703-353 | Form: TABLET
Manufacturer: Silver Star Brands
Category: homeopathic | Type: HUMAN OTC DRUG LABEL
Date: 20250101

ACTIVE INGREDIENTS: LOBELIA INFLATA 30 [hp_C]/180 1; GELSEMIUM SEMPERVIRENS ROOT 30 [hp_C]/180 1; ANAMIRTA COCCULUS SEED 30 [hp_C]/180 1; BRYONIA CRETICA SUBSP. DIOICA ROOT 30 [hp_C]/180 1
INACTIVE INGREDIENTS: MAGNESIUM STEARATE; MALTODEXTRIN; SUCROSE

NativeRemedies® VertiFree™ Tablets

HPUS Active Ingredients: Each tablet contains equal parts of: Bryonia 30C, Cocculus 30C, Gelsemium 30C, Lobelia inf 30C.

Uses*

Uses*: Homeopathic remedy for temporary relief of dizziness and nausea.

*Claims based on traditional homeopathic practice, not accepted medical evidence. Not FDA evaluated.

Warnings

Warnings: If symptoms persist or worsen, consult a healthcare professional. If pregnant or breastfeeding, ask a health professional before use. Keep this and all medication out ofreach of children. In an overdose, get medical help or contact an Poison Control Center right away.

Directions

Directions: Chew or dissolve tablet in the mouth. Alternatively, for small babies, crush tablets and sprinkle onto tongue or mix in warm water or soft food. For all ages: Acute: Take 2 tablets every 20 minutes or until symptoms subside. Chronic: Take 2 tables 3 times daily on an empty stomach.

OTHER SAFETY INFORMATION

Tamper resistant for your protection. Use only if seal is intact.

Contains no artificial flavors or colorants. No gluten added. Lactose-free.

Inactive Ingredients:

Inactive Ingredients: Magnesium stearate, Maltodextrin, Sucrose.

KEEP OUT OF REACH OF CHILDREN

Keep this and all medication out of reach of children.

PREGNANCY OR BREAST FEEDING

If pregnant or breastfeeding, ask a health professional before use.

PURPOSE

Temporarily relieves dizziness & nausea*

*Claims based on traditional homeopathic practice, not accepted medical evidence. Not FDA evaluated.